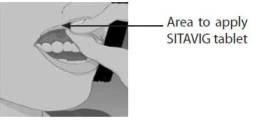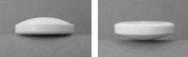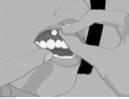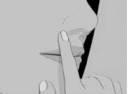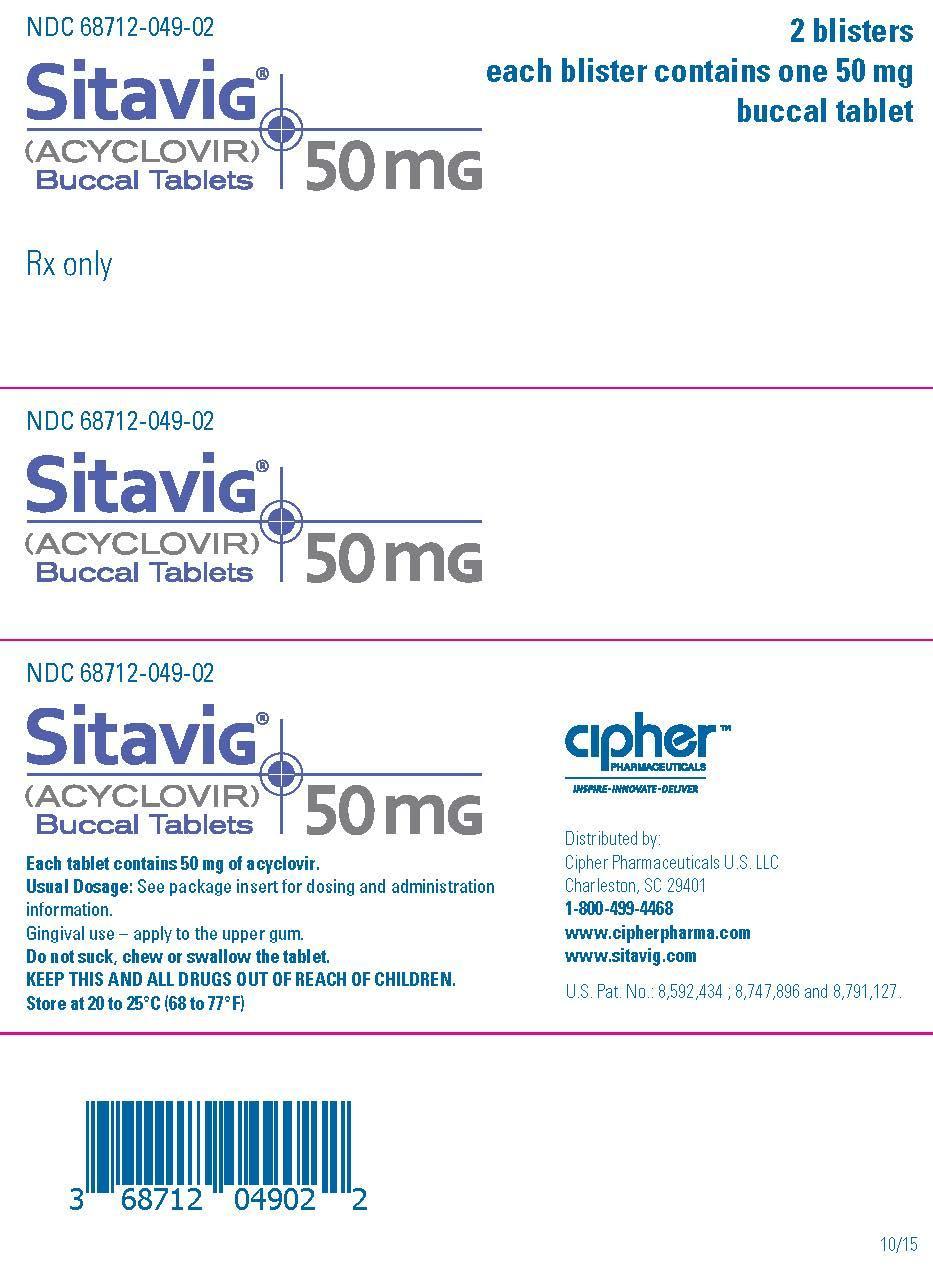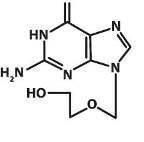 DRUG LABEL: Sitavig
NDC: 68712-049 | Form: TABLET, DELAYED RELEASE
Manufacturer: Cipher Pharmaceuticals US LLC
Category: prescription | Type: HUMAN PRESCRIPTION DRUG LABEL
Date: 20170418

ACTIVE INGREDIENTS: ACYCLOVIR 50 mg/1 1
INACTIVE INGREDIENTS: CELLULOSE, MICROCRYSTALLINE; SODIUM LAURYL SULFATE; POVIDONE; WATER; HYPROMELLOSE 2208 (15000 MPA.S); MAGNESIUM STEARATE; SILICON DIOXIDE

NDC 68712-049-02
Sitavig (ACYCLOVIR) Buccal Tablets 50 mg

HIGHLIGHTS OF PRESCRIBING INFORMATION

These highlights do not include all the information needed to use SITAVIG safely and effectively. See full prescribing information for SITAVIG.

SITAVIG (acyclovir) buccal tablets 50mg

Initial U.S. Approval: 1982

INDICATIONS AND USAGE

SITAVIG is indicated for the treatment of recurrent herpes labialis (cold sores) in immunocompetent adults (1).

DOSAGE AND ADMINISTRATION

- Application of one SITAVIG 50 mg buccal tablet as a single dose to the upper gum (canine fossa) region (2.1).
- SITAVIG should be applied within one hour after the onset of prodromal symptoms and before the appearance of any signs of herpes labailis.
- Do not crush, chew, suck or swallow tablets (2.2)

DOSAGE FORMS AND STRENGTHS

50 mg buccal tablets (3).

CONTRAINDICATIONS

Known hypersensitivity to acyclovir, milk protein concentrate, or any other component of the product (4).

ADVERSE REACTIONS

Most common adverse reactions (> or =1%) are: headache and application site pain (6.1).

To report SUSPECTED ADVERSE REACTIONS, contact Cipher Pharmaceuticals U.S. LLC at 1-800-499-4468 or FDA at 1-800-FDA-1088 or www.fda.gov/medwatch.

DRUG INTERACTIONS

Due to low dose and minimal systemic absorption of SITAVIG, drug interactions are unlikely (7).

USE IN SPECIFIC POPULATIONS

- Nursing Mothers: Caution should be exercised when administered to a nursing woman (8.3).

See 17 for PATIENT COUNSELING INFORMATION AND FDA-Approved Patient Labeling

Revised: 10/2015

FULL PRESCRIBNG INFORMATION: CONTENTS*

1 INDICATIONS AND USAGE

2 DOSAGE AND ADMINISTRATION

2.1 Basic Dosing Information

2.2 Administration Instructions

3 DOSAGE FORMS AND STRENGTHS

4 CONTRAINDICATIONS

6 ADVERSE REACTIONS

6.1 Clinical Trial Experience

7 DRUG INTERACTIONS

8 USE IN SPECIFIC POPULATIONS

8.1 Pregnancy

8.2 Labor and Delivery

8.3 Nursing Mothers

8.4 Pediatric Use

8.5 Geriatric Use

8.6 Immunocompromised Patients

10 OVERDOSAGE

11 DESCRIPTION

12 CLINICAL PHARMACOLOGY

12.1 Mechanism of Action

12.3 Pharmacokinetics

12.4 Microbiology

13 NONCLINICAL TOXICOLOGY

13.1 Carcinogenesis, Mutagenesis, Impairment ofFertility

14 CLINICAL STUDIES

16 HOW SUPPLIED/STORAGE AND HANDLING

17 PATIENT COUNSELING INFORMATION

17.1 Instructions for Use

17.2 Adverse Reactions

* Sections or subsections omitted from the full prescribing informationare not listed.

1 INDICATIONS AND USAGE

SITAVIG is indicated for the treatment of recurrent herpes labialis (cold sores) in immunocompetent adults.

2 DOSAGE AND ADMINISTRATION

2.1 Basic Dosing Information

One SITAVIG 50 mg buccal tablet should be applied as a single dose to the upper gum region (canine fossa).

2.2 Administration Instructions

SITAVIG should be applied within one hour after the onset of prodromal symptoms and before the appearance of any signs of herpes labialis lesions. The tablet should be applied with a dry finger immediately after taking it out of the blister. The tablet should be placed to the upper gum just above the incisor tooth (canine fossa) and held in place with a slight pressure over the upper lip for 30 seconds to ensure adhesion. For comfort the rounded side should be placed to the upper gum, but either side of the tablet can be applied. Tablet should be applied on the same side of the mouth as the herpes labialis symptoms.

Once applied, SITAVIG stays in position and gradually dissolves during the day. [See Clinical Pharmacology (12.3)]. In addition,

- SITAVIG should not be crushed, chewed, sucked or swallowed.
- Food and drink can be taken normally when SITAVIG is in place. Avoid any situation which may interfere with adhesion of the tablet such as chewing gum, touching or pressing the tablet after placement, wearing upper denture, and brushing teeth. If the teeth need to be cleaned while the tablet is in place, rinse the mouth gently. Drink plenty of liquids in the case of dry mouth.
- If SITAVIG does not adhere or falls off within the first 6 hours, the same tablet should be repositioned immediately. If the tablet cannot be repositioned, a new tablet should be placed.
- If SITAVIG is swallowed within the first 6 hours, the patient should drink a glass of water and a new tablet should be applied. [See Patient Counseling Information (17)].
- SITAVIG does not need to be reapplied if the tablet falls out or is swalloed after the first 6 hours

3 DOSAGE FORMS AND STRENGTHS

SITAVIG is a buccal tablet containing 50 mg of acyclovir. SITAVIG tablets are round, off-white tablets, with a rounded side and a flat side. The tablets are marked with an "AL21" on the flat side.

4 CONTRAINDICATIONS

SITAVIG is contraindicated in patients with known hypersensitivity (e.g., anaphylaxis) to acyclovir, milk protein concentrate, or any other component of the product.

6 ADVERSE REACTIONS

6.1 Clinical Trial Experience

Because clinical trials are conducted under widely varying conditions, adverse reaction rates observed in the clinical trials of a drug cannot be directly compared to rates in the clinical trials of another drug and may not reflect the rates observed in clinical practice.

The overall safety of SITAVIG was assessed in 378 adult subjects having at least 4 herpes labialis episodes the previous year.

One randomized, double-blind, placebo controled trial was conducted in patients with recurrent herpes labialis (cold sores). In this trial, 378 HSV infected subjects used SITAVIG as a single dose, and 397 subjects used placebo.

Selected treatment emergent adverse events without regard to causality and reported in at least 1% of patients can be seen in Table 1.

Table 1:

Selected Treatment Emergent Adverse Events reported in at least 1% of patients
Event | SITAVIG; N = 378 | Placebo; N = 397
Nervous System Disorders; Headache; Dizziness; Lethargy | 3%; 1%; 1% | 3%; 1%; 0
Gastrointestinal system Disorders; Gingival Pain; Aphthous Stomatitis | 1%; 1% | 0.38%; 0
Administration Site Conditions; Application Site Pain; Application Site Irritation | 1%; 1% | 1%; 0
Skin and Subcutaneous Disorders; Erythema; Rash | 1%; 1% | 0.3%; 0.3%

The treatment emergent adverse events considered related to the treatment that occurred in greater than or equal to 1% of patients included headache (1% SITAVIG vs. 2% placebo) and application site pain (1% both arms). There was no discontinuation of SITAVIG due to adverse drug reactions. Most treatment related to adverse events were mild or moderate in severity. One report of headache from both treatment arms was classified as severe.

7 DRUG INTERACTIONS

No interaction studies have been performed with SITAVIG. Acyclovir is primarily eliminated unchanged in the urine via active tubular secretion. Drugs administered concomitantly that compete with tubular secretion may increase acyclovir plasma concentrations. However, due to the low dose and minimal systemic absorption of SITAVIG, systemic drug interactions are unlikely.

8 USE IN SPECIFIC POPULATIONS

8.1 Pregnancy

Pregnancy Category B

No studies with SITAVIG have been performed in pregnant women. Systemic exposure of acyclovir following buccal administration of SITAVIG is minimal. SITAVIG should be used during pregnancy only if the potential benefit outweighs the potential risk to the fetus. There are no adequate and well-controlled studies of systemic acyclovir in pregnant women. A prospective epidemiologic registry of acyclovir use during pregnancy between 1984 and 1999 followed 749 pregnancies in women exposed to systemic acyclovir during the first trimester of pregnancy resulting in 756 outcomes. The occurrence rate of birth defects approximated that found in the general population. However, the size of the registry was insufficient to evaluate the risk for less common defects or to permit reliable or definitive conclusions regarding the safety of acyclovir in pregnant women and their developing fetuses.

Animal Data

Animal reproduction studies have not been conducted with SITAVIG. Acyclovir was not teratogenic in the mouse, rabbit or rat at exposures greatly in excess of human exposure.

8.2 Labor and Delivery

SITAVIG should not be administered during labor and delivery as there is no experience with SITAVIG.

8.3 Nursing Mothers

It is not known whether topically applied acyclovir is excreted in breast milk. Systemic exposure following buccal administration is minimal. After oral administration of acyclovir, concentrations have been documented in breast milk in 2 women and ranged from 0.6 to 4.1 times the corresponding plasma levels. These concentrations would potentially expose the nursing infant to a dose of acyclovir up to 0.3 mg/kg/day. There is no experience with SITAVIG in nursing mothers. SITAVIG should be administered to a nursing mother with caution.

8.4 Pediatric Use

Safety and effectiveness of SITAVIG in pediatric patients have not been established. The ability of pediatric patients to comply with the application instructions has not been evaluated. Use in younger children is not recommended due to potential risk of choking.

8.5 Geriatric Use

Clinical studies of SITAVIG did not include sufficient numbers of subjects aged 65 and over to determine whether they respond differently from younger subjects.

8.6 Immunocompromised Patients

The safety of SITAVIG has not been studied in immunocompromised subjects.

10 OVERDOSAGE

Acyclovir absorption and systemic exposure following application of SITAVIG are minimal. Overdose is therefore unlikely [see Clinical Pharmacology (12.3)] .

Symptomatic and supportive care is the basis for management.

11 DESCRIPTION SECTION

SITAVIG (acyclovir) buccal tablet is applied topically to the gum and releases acyclovir as the buccal tablet gradually dissolves [see Clinical
Pharmacology (12.3)] . Acyclovir is a synthetic purine nucleoside analogue active against herpes viruses. The chemical name of acyclovir is 2-amino-1,9-dihydro-9-[(2-hydroxyethoxy)methyl]-6H-purin-6-one; it has a molecular formula of C8H11N5O3 and a molecular weight of 225. The structural formula is shown in Figure 1.

Acyclovir drug substance is a white or almost white crystalline powder. SITAVIG contains 50 mg of acyclovir, USP and the following inactive
ingredients: hypromellose, USP; milk protein concentrate; sodium lauryl sulfate, NF; magnesium stearate, NF; microcrystalline cellulose,
NF; povidone, USP; colloidal silicon dioxide, NF.

12 CLINICAL PHARMACOLOGY

12.1 Mechanism of Action

Acyclovir is an antiviral drug [see Microbiology (12.4)].

12.3 Pharmacokinetics

Absorption and Distribution

Salivary

Single dose application of SITAVIG containing 50 mg of acyclovir to the buccal mucosa in 12 healthy volunteers provided mean maximum
salivary concentrations of 440 μg/mL 8 hours after application of the tablet. The pharmacokinetic parameters of acyclovir in the saliva of
healthy volunteers are provided in Table 2 .

Table 2: Pharmacokinetic (PK) Parameters of Acyclovir in Saliva Following Application of a Single SITAVIG 50 mg Tablet in Healthy Volunteers (N = 12)

Salivary PK Parameters(N = 12) Mean ±SD (Min - Max)

AUC0-24h (mcg.h/mL) 2900 ± 2400 (849 - 9450)
Cmax (mcg/mL) 440 ± 241 (149 – 959)
Tmax (hour) 7.95 ± 4.08 (3.07 – 18.05)

In the Phase 3 study, the levels of acyclovir in saliva were measured within 24 hours of SITAVIG application in 56 patients with recurrent
herpes labialis (mean value 88.1 micrograms per mL) and were within the range of those observed in the PK study in healthy volunteers.
In healthy volunteers, the median duration of buccal adhesion was 14 hours following application of a single SITAVIG 50 mg tablet.

Plasma

Plasma concentrations of acyclovir were measured in 12 healthy volunteers after a single-dose application of SITAVIG 50 mg buccal tablet. Acyclovir concentrations had a delayed appearance (undetectable at 5 hours) and were below the concentrations required for antiviral activity (range: 17.5 to 55.3 nanogram per mL).

Metabolism and Excretion

Acyclovir is metabolized to 9-[(carboxymethoxy)methyl]guanine (CMMG) and 8-hydroxy-acyclovir (8-OH-ACV) by oxidation and hydroxylation, and is primarily excreted unchanged by the kidneys.

Food Effect

There was no formal food effect study conducted with SITAVIG; however, in clinical studies patients were allowed to eat and drink while taking SITAVIG.

12.4 Microbiology

Mechanism of Action

Acyclovir is a synthetic purine nucleoside that is phosphorylated intracellularly by the viral encoded thymidine kinase (TK) of HSV into acyclovir monophosphate, a nucleotide analogue. The monophosphate is further converted into diphosphate by cellular guanylate kinase and into triphosphate by a number of cellular enzymes. In a biochemical reaction, acyclovir triphosphate inhibits replication of herpes viral DNA by competing with nucleotides for binding to the viral DNA polymerase and by incorporation into and termination of the growing viral DNA chain. The cellular thymidine kinase of normal, uninfected cells does not use acyclovir effectively as a substrate, hence toxicity to mammalian host cells is low.

Antiviral activity

The quantitative relationship between the cell culture susceptibility of herpes viruses to antivirals and the clinical response to therapy
has not been established in humans, and virus sensitivity testing has not been standardized. Sensitivity testing results, expressed as
the concentration of drug required to inhibit by 50% the growth of virus in cell culture (EC50), vary greatly depending upon a number
of factors. Using plaque-reduction assays on Vero cells, the median EC50 value of acyclovir against clinical herpes virus isolates (subjects
receiving placebo) was 1.3 μM (range: < 0.56 to 3.3 μM).

Drug Resistance

Resistance of HSV to acyclovir can result from qualitative and quantitative changes in the viral TK and/or DNA polymerase. Clinical
isolates of HSV with reduced susceptibility to acyclovir have been recovered from immunocompromised subjects, especially with
advanced HIV infection. While most of the acyclovir-resistant mutant isolates from immunocompromised subjects thus far have been
found to be TK-deficient, other mutant isolates involving the viral TK gene (TK partial and TK altered) or DNA polymerase have been
identified. TK-negative mutants may cause severe disease in infants and immunocompromised adults.

The possibility of viral resistance to acyclovir should be considered in immunocompromised subjects who show poor clinical response during therapy.

13 NONCLINICAL TOXICOLOGY

13.1 Carcinogenesis, Mutagenesis, Impairment of Fertility

Systemic exposure following buccal administration of acyclovir is minimal. Results from previous studies of carcinogenesis, mutagenesis
and fertility for acyclovir are not included in the full prescribing information for SITAVIG due to the minimal exposure that results
from buccal administration. Information on these studies following systemic exposure is available in the full prescribing information for
acyclovir products approved for oral and parenteral administration.

14 Clinical Studies

Study in Patients with Recurrent Herpes Labialis (cold sores)

The efficacy and safety of SITAVIG was evaluated in a randomized, double-blind, placebo-controlled, patient-initiated, multicenter trial comparing SITAVIG 50 mg administered as a single dose (n = 378) to placebo (n = 397) in patients with recurrent herpes labialis (cold sores). A total of 376 SITAVIG treated patients and 395 placebo treated patients were included in the Intent to Treat (ITT) efficacy population defined as all patients who took study treatment and who had a start date and time of treatment initiation recorded. The mean age was 41.0 years (range: 18-80 years) and the majority of patients were female (68.6%), and Caucasian (94.9%). All patients had at least 4 herpes episodes in the previous year of whom 68.4% had ≥ 5 episodes. Patients were instructed to initiate treatment within one hour after the onset of prodromal symptoms and before the appearance of any signs of herpes labialis lesions by applying the tablet to the buccal mucosa in the canine fossa. If the tablet was detached within the first 6 hours, subjects were instructed to reapply a tablet.

The mean and median durations of the recurrent herpes labialis episode (ITT population, n=771) were approximately half a day shorter in patients treated with SITAVIG compared with patients treated with placebo.

16 HOW SUPPLIED/STORAGE AND HANDLING

SITAVIG 50 mg buccal tablets are supplied as off-white tablets containing 50 mg of acyclovir. SITAVIG tablets have a rounded side and
a flat side. SITAVIG tablets are packaged in blisters (NDC 68712-049-02).

SITAVIG should be stored at 20 to 25°C (68 to 77°F) [see USP controlled room temperature]; excursions between 15 and 30°C (59-86°F)
permitted at room temperature. Protect from moisture, and keep out of reach of children.

17 PATIENT COUNSELING INFORMATION

Patients should be informed that SITAVIG is not a cure for cold sores. See FDA-approved patient labeling (Patient Information and Instructions for Use).

17.1 Instructions For Use

Read the Instructions for Use that comes with SITAVIG before you start using it. Talk to your doctor or pharmacist if you have any questions.

Important:
SITAVIG should be applied to the area of the upper gum above the incisor tooth.
SITAVIG tablets should not be crushed, sucked, chewed or swallowed.

If it comes out before 6 hours have gone by, reapply it.
If this does not work then a new tablet should be applied.
It should not be applied to the inside of the lip or cheek.
• Tablet should be applied on the same side of the mouth as the herpes labialis symptoms.
• Do not remove SITAVIG if it sticks to your upper gum. If SITAVIG does not stick or falls off of your upper gum within the first 6
hours that you apply it, place it back onto your upper gum. If it still does not stick, replace it with a new SITAVIG tablet.
• Do not re-apply SITAVIG if it falls out or you swallow it after it has been in place 6 hours or longer.
• If you swallow SITAVIG within the first 6 hours of applying it, drink a glass of water and place a new SITAVIG tablet onto your upper gum.

17.2 Adverse Reactions

Patients may experience adverse reactions including headache, and application site pain.

Patient Information

SITAVIG (SIT-a-vig) (acyclovir) buccal tablets

What is SITAVIG?
• SITAVIG is a prescription medicine used to treat cold sores (herpes labialis) in adults with normal immune systems.
• It is not known if SITAVIG is safe and effective in children.

Who should not use SITAVIG?
Do not use SITAVIG if you are allergic to:
• acyclovir or any of the ingredients in SITAVIG. See the end of this leaflet for a complete list of ingredients in SITAVIG.
• milk protein concentrate

Before using SITAVIG, tell your healthcare provider about all of your medical conditions, including if you:
• are pregnant or plan to become pregnant. It is not known if SITAVIG will harm your unborn baby.
• are breastfeeding or plan to breastfeed. It is not known if SITAVIG passes into your breast milk.
• Tell your healthcare provider about all the medicines you take, including prescription or over-the-counter medicines, vitamins, or herbal supplements.

How should I use SITAVIG?
See the detailed Instructions for Use for informationabout how to use SITAVIG.
• Use SITAVIG exactly as your healthcare provider tells you to use it.
• Use SITAVIG within 1 hour after you have the first symptom of a cold sore, such as itching, redness, burning, or tingling,
and before a cold sore appears.
• You may eat and drink while using SITAVIG.
• Do not crush, chew, suck, or swallow SITAVIG tablets.
• SITAVIG will slowly dissolve over time while in your mouth and should be left in place.
• Gently rinse your mouth with water to clean your teeth while SITAVIG is in place.
• Drink more liquids if your mouth becomes dry while using SITAVIG.

What should I avoid while using SITAVIG?
You should avoid activities that may prevent SITAVIG from sticking to your gum, including: touching or pressing SITAVIG
after you apply it, wearing upper dentures, chewing gum, and brushing your teeth during the treatment day.

What are the possible side effects of SITAVIG?
The most common side effects of SITAVIG include: headache and pain where SITAVIG is applied.
These are not all the possible side effects of SITAVIG. Call your doctor for medical advice about side effects. You may
report side effects to FDA at 1-800-FDA-1088.

How should I store SITAVIG?
• Store SITAVIG between 68°F to 77°F (20°C to 25°C). Keep SITAVIG tablets dry.

Keep SITAVIG and all medicines out of the reach of children.

General information about the safe and effective use of SITAVIG
Medicines are sometimes prescribed for purposes other than those listed in a Patient Information leaflet. Do not use
SITAVIG for a condition for which it was not prescribed. Do not give SITAVIG to other people, even if they have the same
symptoms that you have. It may harm them. You can ask your pharmacist or healthcare provider for information about
SITAVIG that is written for health professionals.

What are the ingredients in SITAVIG?
Active ingredient: acyclovir
Inactive ingredients: hypromellose, milk protein concentrate, sodium lauryl sulfate, magnesium stearate,microcrystalline cellulose, povidone, colloidal silicon dioxide.

Manufactured By: Farméa,10 rue Bouché Thomas, ZAC d’orgemont, 49 000 Angers - France

For more information call 1-800-499-4468.

This Patient Information has been approved by the U.S. Food and DrugAdministration. Issue: April/2013 Reference ID: 3292406

INSTRUCTIONS FOR USE

SITAVIG (SIT-a-vig) (acyclovir) buccal tablets

Read the Instructions for Use that comes with SITAVIG before you start using it. Talk to your healthcare provider or pharmacist if you have any questions.

Important:
• SITAVIG should be applied within 1 hour after you have the first symptom of a cold sore, such as itching, redness, burning, or tingling, and before a cold sore appears.
• SITAVIG should be applied on the same side of your mouth as the cold sore symptoms.
• SITAVIG should be applied to your upper gum, just above your incisor tooth.
• SITAVIG should not be applied to the inside of your lip or your cheek.
• If SITAVIG does not stick to your upper gum or falls off of your upper gum within the first 6 hours after you apply it, the same tablet should be placed back onto your upper gum right away. If this SITAVIG tablet does not stay in place, apply another SITAVIG tablet to your upper gum.
• Do not re-apply SITAVIG if it falls out or you swallow it after it has been in place 6 hours or longer.
• If you swallow SITAVIG within the first 6 hours of applying it, drink a glass of water and place a new SITAVIG tablet onto your upper gum.

How to apply Sitavig

Step 1: Before you apply SITAVIG, find the area on your upper gum, just above either the left or the right incisor. The incisor tooth is the tooth just to the right or left of your two front teeth (See Figure A). This is where you should apply SITAVIG.

Figure A

Step 2:

Peel back the cover of the blister pack. Take 1 SITAVIG out of the blister pack. When removed from the blister pack, SITAVIG must be used right away. SITAVIG is round on one side and flat on the other side (See Figure B).

Figure B

Step 3: Place the flat side of SITAVIG on your dry fingertip. Apply the round side of SITAVIG to your upper gum (See Figure C). The flat side will be facing the inside of your lip.

Figure C

Step 4: Hold SITAVIG in place by applying a slight pressure with your finger on the outside of your upper lip, over the area where SITAVIG is placed, for 30 seconds. This will help SITAVIG stick to your gum (See Figure D).

Figure D

Step 5: Leave the SITAVIG tablet in place until it dissolves.

This Instructions for Use has been approved by the U.S. Food and Drug Administration.
Manufactured By:
Farméa
10 rue Bouché Thomas
ZAC d’orgemont
49 000 Angers - France

Distributed By:

Cipher Pharmaceuticals U.S. LLC

Charleston, SC 29401

1-800-449-4468

www.cipherpharma.com

www.sitavig.com

U.S. Pat. No.: 8,592,434, 8,747,896 and 8,791,127.
©2013 Cipher Pharmaceuticals U.S. LLC
Revised: 10/2015 SIT-PI-0417